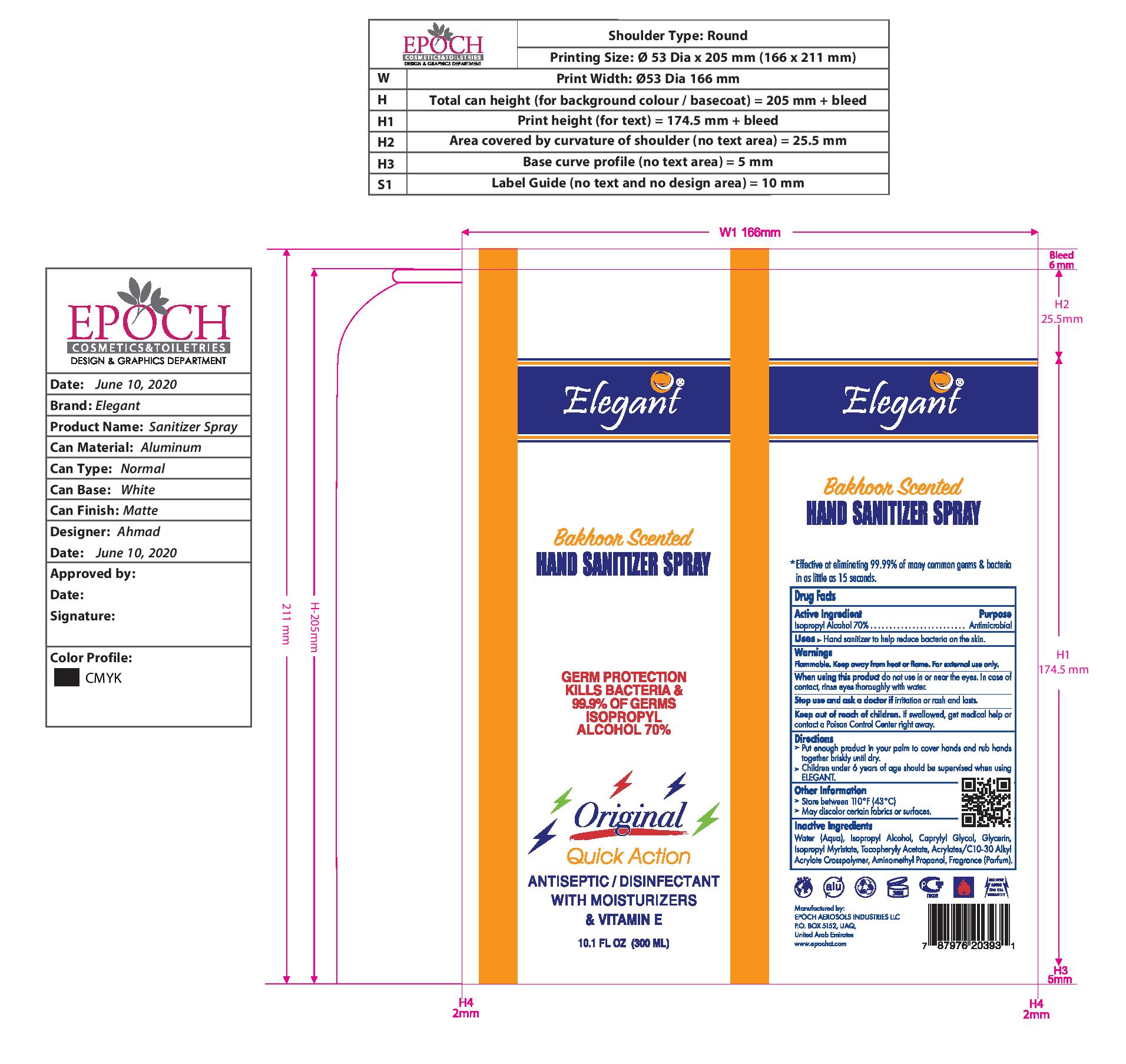 DRUG LABEL: Elegant Bakhoor Scented Hand Sanitizer
NDC: 80309-004 | Form: SPRAY
Manufacturer: EPOCH Cosmetics and Toiletries Industries LLC
Category: otc | Type: HUMAN OTC DRUG LABEL
Date: 20200902

ACTIVE INGREDIENTS: ISOPROPYL ALCOHOL 70 mL/100 mL
INACTIVE INGREDIENTS: GLYCERIN; WATER; ISOPROPYL MYRISTATE; ETHYLENE GLYCOL; PROPANE; BUTANE

Active Ingredient(s)

Isopropyl Alcohol 70%

Purpose

Antimicrobial

Use

Hand Sanitizer to help reduce bacteria on the skin.

Warnings

For external use only. Flammable. Keep away from heat or flame

When using this product do not use in or near the eyes. keep out of eyes, ears, and mouth. In case of contact with eyes, rinse eyes thoroughly with water.

Stop use and ask a doctor if irritation or rash and lasts.

Keep out of reach of children. If swallowed, get medical help or contact a Poison Control Center right away.

Directions

- Put enough product in your palm to cover hands and rub hands together briskly until dry
- Children under 6 years of age be supervised when using ELEGANT.

Other information

- Store between 110F (43C)
- May discolor certain fabrics

Inactive ingredients

Water (Aqua), Isopropyl Alcohol, Glycerin, Isopropyl Myristate, Tocopheryl Acetate, Aminomethyl Propanol, Fragrance (Parfum), Propane and Butane.